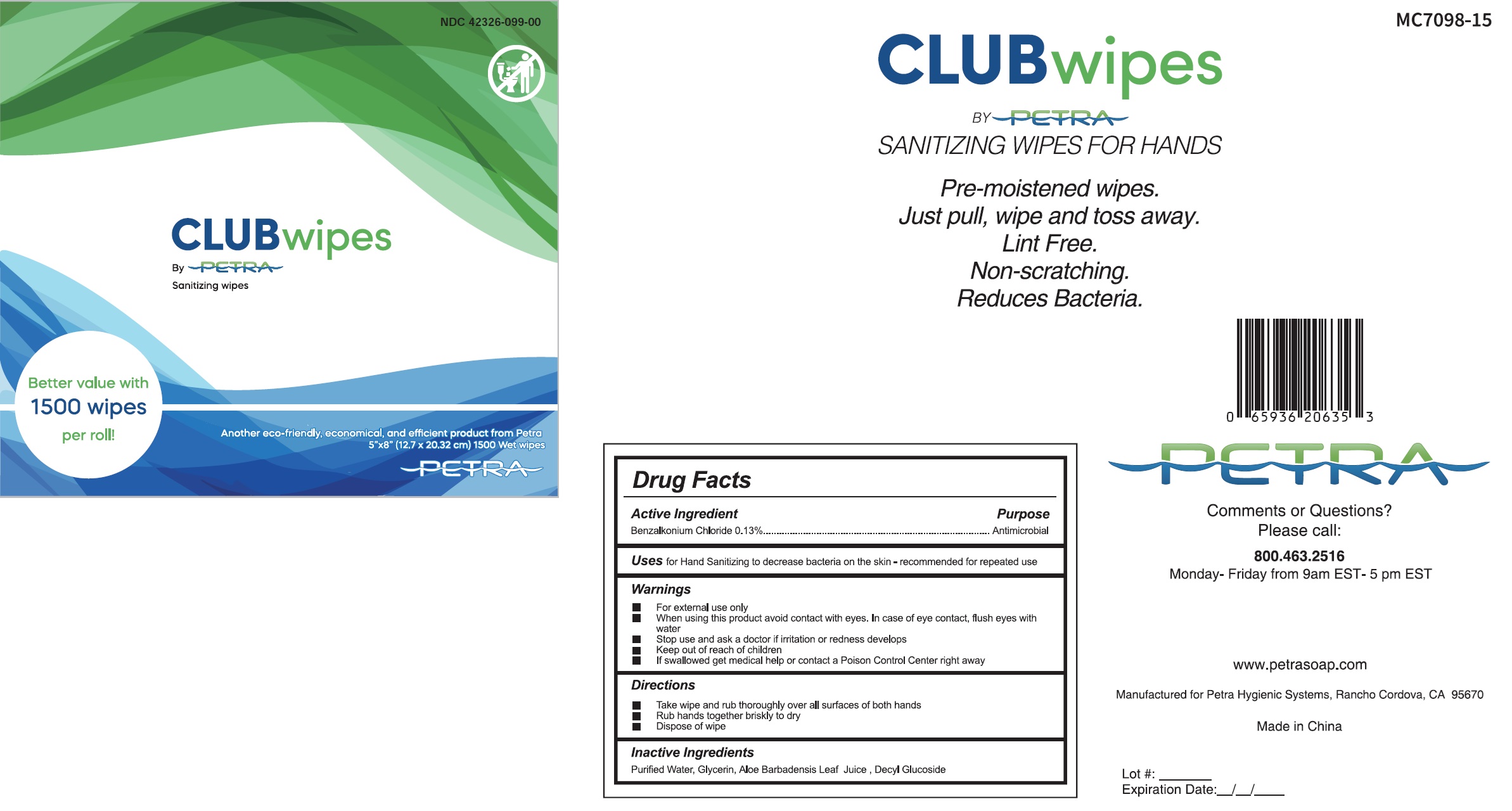 DRUG LABEL: CLUB Wipes Sanitizing Wipes for Hands
NDC: 42326-099 | Form: CLOTH
Manufacturer: Petra Hygienic Systems International Limited
Category: otc | Type: HUMAN OTC DRUG LABEL
Date: 20250717

ACTIVE INGREDIENTS: BENZALKONIUM CHLORIDE 1.3 mg/1 g
INACTIVE INGREDIENTS: GLYCERIN; ALOE VERA LEAF; DECYL GLUCOSIDE; WATER

CLUB Wipes Sanitizing Wipes for Hands

Active Ingredient

Benzalkonium Chloride 0.13%

Purpose

Antimicrobial

Uses

for Hand Sanitizing to decrease on the kin - recommended for repeated use

Warnings

- For external use only

When using this product

- avoid contact with eyes. In case of eye contact, flush eyes with water

Stop use and ask a doctor

- if irritation or redness develops

Keep out of reach of chidlren

- If swallowed get medical help or contact a Poison Control Center right away

Directions

- Take wipe and rub thoroughly over all surfaces or both hands
- Rub hands together briskly to dry
- Dispose of wipe

Inactive Ingredients

Purified Water, Glycerin, Aloe Barbadensis Leaf Juice, Decyl Glucoside